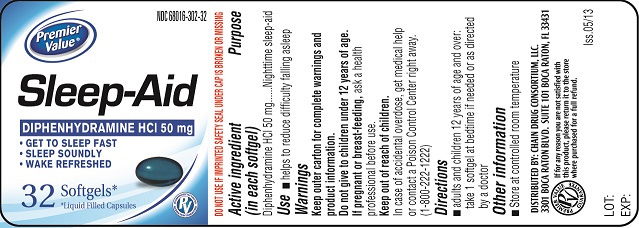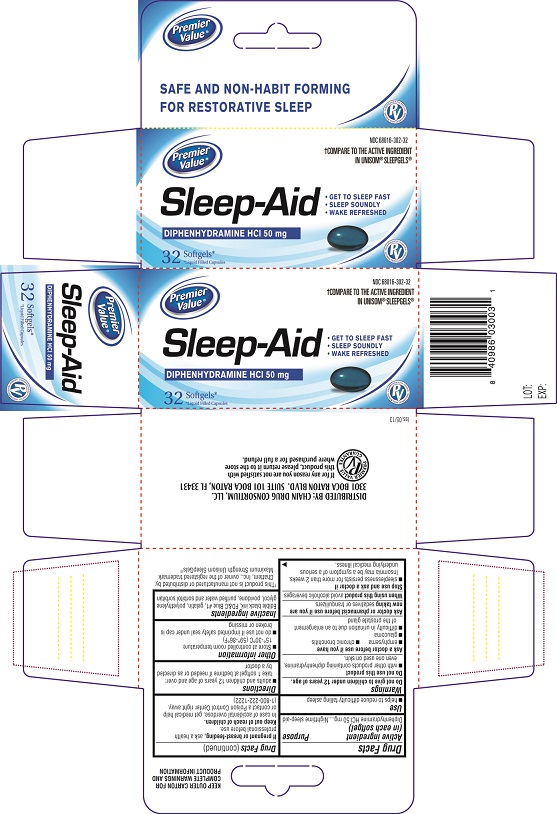 DRUG LABEL: Premier Value Sleep-Aid
NDC: 68016-302 | Form: CAPSULE
Manufacturer: Chain Drug Consortium LLC
Category: otc | Type: Human OTC Drug Label
Date: 20130530

ACTIVE INGREDIENTS: DIPHENHYDRAMINE HYDROCHLORIDE 50 mg/1 1
INACTIVE INGREDIENTS: FD&C BLUE NO. 1; GELATIN; WATER; SORBITAN; SORBITOL; POLYETHYLENE GLYCOL 400; POVIDONE K30

ACTIVE INGREDIENT(S)

Diphenhydramine HCl 50 mg

PURPOSE

Nighttime sleep- aid

USE(S)

- helps to reduce difficulty falling asleep

WARNINGS

Do not give to children under 12 years of age.

DO NOT USE

- With other products containing diphenhydramine, even one used on skin.

ASK A DOCTOR BEFORE USE IF

- emphysema
- chronic bronchitis
- glaucoma
- difficulty in urination due to an enlargement of the prostate gland

ASK A DOCTOR OR PHARMACIST BEFORE USE IF

Sedatives or tranquilizers

WHEN USING THIS PRODUCT

Avoid alcoholic beverages

STOP USE AND ASK DOCTOR IF

- Sleeplessness persists for more than 2 weeks. Insomnia may be a symptom of a serious underlying medical illness.

PREGNANCY/BREASTFEEDING

Ask a health professional before use.

KEEP OUT OF REACH OF CHILDREN

In case of accidental overdose, get medical help or contact a Poison Control Center right away (1-800-222-1222).

DIRECTIONS

- adults and children 12 years of age and over: take 1 softgel at bedtime if needed or as directed by a doctor

STORAGE

- Store at controlled room temperature 15°-30°C (59°-86°F)
- do not use if imprinted safety seal under cap is broken or missing
- *This product is not manufactured or distributed by Chattem, Inc., owner of the registered trademark Maximum Strength Unisom SleepGels®

INACTIVE INGREDIENTS

Gelatin, Sorbitol, Sorbitan, FD&C Blue No. 1, Water, Polyethylene Glycol 400, Povidone K-30

PRINCIPAL DISPLAY PANEL

Carton Label PDP
NDC # 68016-302-32
Sleep-Aid
DIPHENHYDRAMINE HCL 50 mg
GET TO SLEEP FAST
SLEEP SOUNDLY
WAKE REFRESHED
32 Softgels
Bottle Label PDP
NDC # 68016-302-32
Sleep-Aid
DIPHENHYDRAMINE HCL 50 mg
GET TO SLEEP FAST
SLEEP SOUNDLY
WAKE REFRESHED
32 Softgels